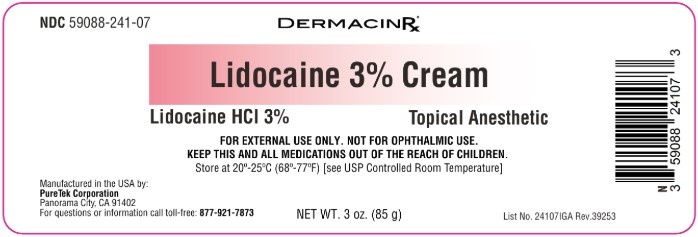 DRUG LABEL: Lidocaine 3%
NDC: 59088-241 | Form: CREAM
Manufacturer: PureTek Corporation
Category: otc | Type: HUMAN OTC DRUG LABEL
Date: 20250812

ACTIVE INGREDIENTS: LIDOCAINE HYDROCHLORIDE 30 mg/1 g
INACTIVE INGREDIENTS: MINERAL OIL; CETEARYL ALCOHOL; SODIUM PHOSPHATE; PROPYLENE GLYCOL; GLYCERIN; WATER; PROPYLPARABEN; METHYLPARABEN; PETROLATUM; CALCIUM ACETATE; CETEARETH-20

NDC 59088-241 Lidocaine 3% Cream

Active Ingredient

Lidocaine HCl 3%

Purpose

Topical Analgesic

Uses

For the temporarily relief of pain and itching associated with:
•minor burns •sunburn •minor cuts •scrapes •insect bites •minor skin irritations •rashes due to poison ivy, poison oak, or poison sumac.

Warnings

• For External Use Only

When using this product:

•Avoid contact with the eyes. •Do not use in large quantities, particularly over raw surfaces or blistered areas.

Stop use and ask a doctor if

• If condition worsens, or if symptoms persist for more than 7 days or clear up and occur again within a few days, discontinue use of this product and consult a licensed healthcare practitioner.

KEEP OUT OF REACH OF CHILDREN

• Keep this and all other drugs out of the reach of children.

Directions:

• Adults and children 2 years of age and older: Apply to affected area not more than 3 to 4 times daily. • Children under 2 years of age: do not use, consult a licensed healthcare practitioner.

Other information

• Store at 20º-25ºC (68º-77ºF) [see USP Controlled Room Temperature]

Inactive ingredients:

Aqua (Purified Water), Calcium Acetate, Ceteareth-20, Cetearyl Alcohol, Glycerin, Methylparaben, Mineral Oil, Petrolatum, Propylene Glycol, Propylparaben, Sodium Phosphate.